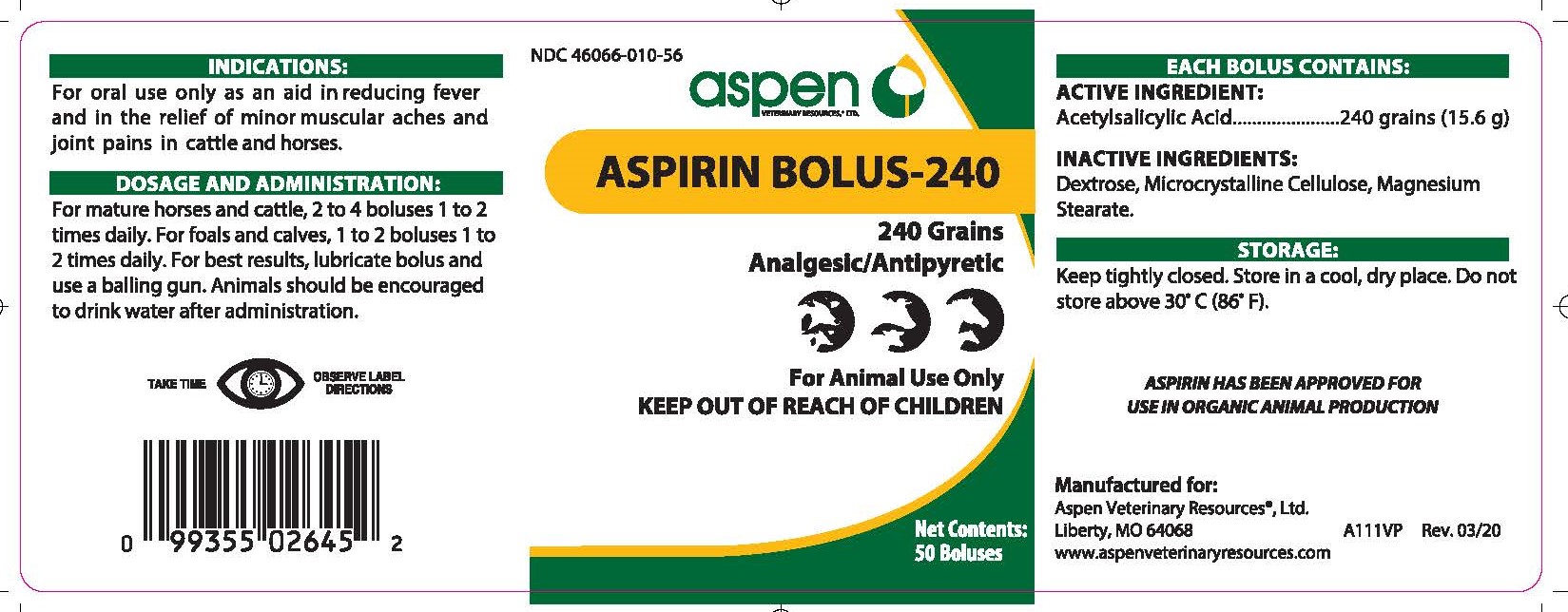 DRUG LABEL: Aspirin Bolus-240
NDC: 46066-010 | Form: TABLET
Manufacturer: Aspen Veterinary Resources, Ltd
Category: animal | Type: OTC ANIMAL DRUG LABEL
Date: 20250113

ACTIVE INGREDIENTS: ASPIRIN 15.6 g/1 1

Indications:

For oral use only as an aid in reducing fever and in the relief of minor muscular aches and joint pains in cattle and horses.

INDICATIONS AND USAGE

Analgesic/Antipyretic

Dosage and Administration:

For mature horses and cattle, 2 to 4 boluses 1 to 2 times daily. For foals and calves, 1 to 2 bolues 1 to 2 times daily. For best results, lubricate bolus and use a balling gun. Animals should be encouraged to drink water after administration.

Each bolus contains: Active Ingredient:

Acetylsalicylic Acid............240 grains (15.6g)

Each bolus contains: Inactive Ingredients:

Dextrose, Microcrystalline Cellulose, Magnesium Stearate

Storage:

Keep tightly closed. Store in a cool, dry place. Do not store about 30°C (86°F).

KEEP OUT OF REACH OF CHILDREN

For Animal Use Only

KEEP OUT OF REACH OF CHILDREN

PACKAGE LABEL

Add image transcription here...